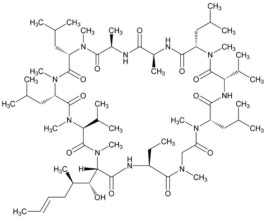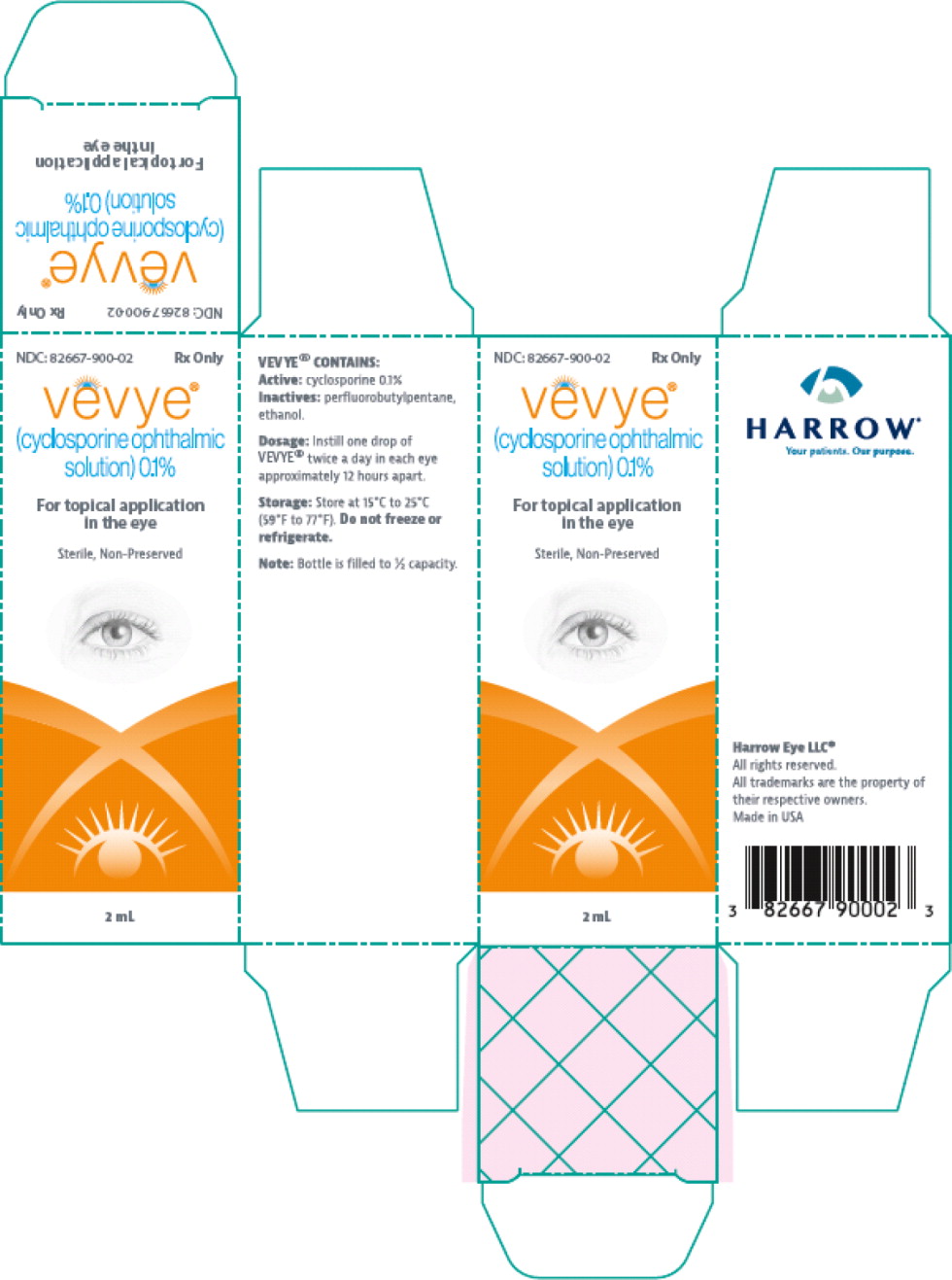 DRUG LABEL: VEVYE
NDC: 82667-900 | Form: SOLUTION/ DROPS
Manufacturer: Harrow Eye, LLC
Category: prescription | Type: HUMAN PRESCRIPTION DRUG LABEL
Date: 20260226

ACTIVE INGREDIENTS: CYCLOSPORINE 1 mg/1 mL
INACTIVE INGREDIENTS: 1,1,1,2,2,3,3,4,4-NONAFLUORONONANE; ALCOHOL

HIGHLIGHTS OF PRESCRIBING INFORMATION

These highlights do not include all the information needed to use VEVYE®safely and effectively. See full prescribing information for VEVYE.
VEVYE (cyclosporine ophthalmic solution) 0.1%,
for topical ophthalmic use
Initial U.S. Approval: 1983

RECENT MAJOR CHANGES

Dosage and Administration (2.2) | 9/2025

1 INDICATIONS AND USAGE

VEVYE (cyclosporine ophthalmic solution) 0.1% is a calcineurin inhibitor immunosuppressant indicated for the treatment of the signs and symptoms of dry eye disease. (1)

2 DOSAGE AND ADMINISTRATION

Instill one drop of VEVYE twice a day in each eye approximately 12 hours apart. (2)

3 DOSAGE FORMS AND STRENGTHS

Ophthalmic solution containing cyclosporine 0.1%. (3)

4 CONTRAINDICATIONS

None. (4)

5 WARNINGS AND PRECAUTIONS

Care should be taken to not touch the eye or other surfaces with the bottle tip to avoid potential for eye injury and/or contamination. (5.1)

6 ADVERSE REACTIONS

The most common adverse reaction following the use of VEVYE were instillation site reactions (8%). (6.1)

To report SUSPECTED ADVERSE REACTIONS, contact

Harrow at 1-833-4HARROW(427769) or FDA at 1-800-FDA-1088 orwww.fda.gov/medwatch.

FULL PRESCRIBING INFORMATION

1 INDICATIONS AND USAGE

VEVYE indicated for the treatment of the signs and symptoms of dry eye disease.

2 DOSAGE AND ADMINISTRATION

2.1 Recommended Dosage

Instill one drop of VEVYE twice a day in each eye approximately 12 hours apart.

2.2 Administration Instructions

Wash hands before using.

Gently pull the lower eyelid downward. Tip the bottle upside down over the eye to allow one drop to dispense on its own into the eye. If a drop does not dispense after a few seconds, gently apply slight pressure to the sides of the bottle while holding over the eye.

Note:You may not feel the drop falling into your eye.

If VEVYE is used with other eye drops, a 15-minute interval between products should occur.

3 DOSAGE FORMS AND STRENGTHS

Clear, colorless non-preserved ophthalmic solution containing cyclosporine 0.1% (1 mg/mL), delivering 0.01 mg of cyclosporine per one drop (0.01 mL).

4 CONTRAINDICATIONS

None.

5 WARNINGS AND PRECAUTIONS

5.1 Potential for Eye Injury and Contamination

To avoid the potential for eye injury and/or contamination, patients should not touch the bottle tip to the eye or other surfaces.

5.2 Use with Contact Lenses

VEVYE should not be administered while wearing contact lenses. If contact lenses are worn, they should be removed prior to administration of the solution. Lenses may be reinserted 15 minutes following administration of VEVYE ophthalmic solution.

6 ADVERSE REACTIONS

6.1 Clinical Trials Experience

Because clinical trials are conducted under widely varying conditions, adverse reaction rates observed in the clinical trials of a drug cannot be directly compared to rates in the clinical trials of another drug and may not reflect the rates observed in practice. In clinical trials with 738 subjects receiving at least 1 dose of VEVYE, the most common adverse reactions were instillation site reactions (8%) and temporary decreases in visual acuity (3%).

8 USE IN SPECIFIC POPULATIONS

8.1 Pregnancy

Risk Summary

There are no adequate and well-controlled studies of VEVYE administration in pregnant women to inform a drug-associated risk. Oral administration of cyclosporine to pregnant rats or rabbits did not produce teratogenicity at clinically relevant doses VEVYE doses are approximately 4,700 times lower than recommended oral doses, with blood concentrations being undetectable after topical administration.

Data

Animal Data

Oral administration of cyclosporine oral solution to pregnant rats or rabbits was teratogenic at maternally toxic doses of 30 mg/kg/day in rats and 100 mg/kg/day in rabbits, as indicated by increased pre- and postnatal mortality, reduced fetal weight and skeletal retardations. These doses (normalized to body weight) were approximately 7,250 and 48,000 times higher than the daily maximum recommended human ophthalmic dose (MRHOD) of 0.67 mcg/kg/day, respectively.

No adverse embryofetal effects were observed in rats or rabbits receiving cyclosporine during organogenesis at oral doses up to 17 mg/kg/day or 30 mg/kg/day, respectively (approximately 4,100 and 14,500 times higher than the MRHOD, respectively).

An oral dose of 45 mg/kg/day cyclosporine (approximately 10,900 times higher than MRHOD) administered to rats from Day 15 of pregnancy until Day 21 postpartum produced maternal toxicity and an increase in postnatal mortality in offspring. No adverse effects in mothers or offspring were observed at oral doses of up to 15 mg/kg/day (3600 times greater than MRHOD).

8.2 Lactation

Risk Summary

Cyclosporine is known to be excreted in human milk following systemic administration but excretion in human milk after topical treatment has not been investigated. VEVYE doses are approximately 4,700 times lower than recommended oral doses of cyclosporine, with blood concentrations being undetectable after topical administration. However, caution should be exercised when VEVYE is administered to a nursing woman.

8.4 Pediatric Use

Safety and effectiveness in pediatric patients below the age of 18 years have not been established.

8.5 Geriatric Use

No overall difference in safety or effectiveness has been observed between elderly and younger patients.

11 DESCRIPTION

VEVYE (cyclosporine ophthalmic solution) 0.1% contains the immunomodulatory agent cyclosporine. Cyclosporine's chemical name is Cyclo[[€-(2S,3R,4R)-3-hydroxy-4-methyl-2-(methylamino)-6-octenoyl]-L-2-aminobutyryl-N-methylglycyl-N-methyl-L-leucyl-L-valyl-N-methyl-L-leucyl-L-alanyl-D-alanyl-N-methyl-L-leucyl-N-methyl-L-leucyl-N-methyl-L-valyl] and it has the following structure:

Structural Formula

Formula: C62H111N11O12, Molecular weight: 1202.6

Cyclosporine is a white powder that is solubilized in perfluorobutylpentane, a semi-fluorinated alkane vehicle. VEVYE is supplied as a 2 mL sterile, clear, colorless, non-aqueous ophthalmic solution for topical ophthalmic use. VEVYE®contains:

- Active: cyclosporine 0.1%
- Inactives: perfluorobutylpentane, ethanol (anhydrous).

The solution does not contain water or anti-microbial preservatives. As a water free product, there is no associated pH and no osmolarity.

12 CLINICAL PHARMACOLOGY

12.1 Mechanism of Action

Cyclosporine, a calcineurin inhibitor, is a relatively selective immunomodulatory drug.

12.3 Pharmacokinetics

Following bilateral topical ocular dosing of one drop of VEVYE twice daily, the blood concentrations of cyclosporine were below the limit of quantification (0.1 ng/mL) at all timepoints.

13 NONCLINICAL TOXICOLOGY

13.1 Carcinogenesis, Mutagenesis, Impairment of Fertility

Carcinogenesis

Evaluation of the potential carcinogenicity of cyclosporine was conducted in male and female mice and rats. In a 78-week oral (diet) mouse study, at doses of 1, 4, and 16 mg/kg/day, evidence of a statistically significant trend was found for lymphocytic lymphomas in females, and the incidence of hepatocellular carcinomas in mid -dose males significantly exceeded the control value.

In a 24-month oral (diet) rat study, conducted at 0.5, 2, and 8 mg/kg/day, pancreatic islet cell adenomas significantly exceeded the control rate in the low dose level. The hepatocellular carcinomas and pancreatic islet cell adenomas were not dose related. The low doses in mice and rats were approximately 120 times higher than the maximum recommended human ophthalmic dose (0.67 mcg/kg/day), normalized to body surface area.

Mutagenesis

In genetic toxicity tests, cyclosporine has not been found to be mutagenic/genotoxic in the Ames Test, the V79 HGPRT Test, the micronucleus test in mice and Chinese hamsters, the chromosome-aberration tests in Chinese hamster bone-marrow, the mouse dominant lethal assay, and the DNA-repair test in sperm from treated mice. Cyclosporine was positive in an in vitro sister chromatid exchange (SCE) assay using human lymphocytes.

Impairment of Fertility

Oral administration of cyclosporine to rats for 12 weeks (male) and 2 weeks (female) prior to mating produced no adverse effects on fertility at doses up to 15 mg/kg/day (approximately 3,600 times higher than the maximum recommended human ophthalmic dose).

14 CLINICAL STUDIES

The safety and efficacy of VEVYE were assessed in a total of 1369 patients with dry eye disease, of which 738 received VEVYE.

In two multicenter, randomized, adequate and well-controlled clinical studies, patients with dry eye disease (CYS-002: NCT02617667 and CYS-004: NCT04523129), treated with VEVYE®were compared to patients treated with vehicle. At Day 29, there was a statistically significant higher percentage of eyes with increases of ≥ 10 mm from baseline in Schirmer wetting. This effect was seen in approximately 10% of VEVYE-treated patients versus approximately 6% of vehicle-treated patients.

Percent of Patients Achieving ≥ 10 mm Improvement from Baseline in Schirmer's Tear Test Score in Study Eyes in Patients with Dry Eye Disease
 | CYS-002 Day 29 |  | CYS-004 Day 29
 | VEVYE N=51 | Vehicle N=51 | VEVYE N=409 | Vehicle N=395
≥ 10 mm increase in tear production (% patients) | 8% | 0% | 11% | 7%
Difference (95% CI) | 7.8% (0.5%, 15.%) |  | 3.9% (0.02%, 7.8%)
p-value versus vehicle | 0.04 |  | 0.05

16 HOW SUPPLIED/STORAGE AND HANDLING

VEVYE is a sterile, clear, colorless non-aqueous ophthalmic solution packaged in multiple-dose eye drop bottles delivering single drops of approximately 0.01 mL volume. Each unit contains 2 mL of VEVYE in a 5 mL transparent squeezable polypropylene bottle with a transparent polyethylene tip and a white polyethylene cap with tamper-evident ring.

NDC 82667-900-02

Storage and Handling

Do not use if tamper-evident ring attached to the white cap is not intact. After first opening the tamper-evident ring of the cap remains on the bottle neck. Retain the cap and keep the bottle tightly closed when not in use.

Store at 15°C to 25°C (59°F to 77°F). Do not freeze or refrigerate. After opening, VEVYE can be used until the expiration date on the bottle.

17 PATIENT COUNSELING INFORMATION

Advise patients to read the FDA-approved patient labeling (Instructions for Use).

Risk of Contamination

Advise patients to wash their hands well before each use. Advise patients not to allow the dropper tip to touch the eye or any other surface, as this may contaminate the solution [see Warning and Precautions (5.1)] .

Contact Lens Wear

Contact lenses should be removed prior to instillation of VEVYE and may be reinserted 15 minutes following administration [see Warning and Precautions (5.2)] .

HARROW®
Distributed by
Harrow Eye, LLC
Nashville, TN 37215
USA
© 2024

Principal Display Panel - 2 mL Carton Label

NDC: 82667-900-02 Rx Only

vevye®

(cyclosporine ophthalmic
soliton) 0.1%

For topical application
In the eye

Sterile, Non-Preserved

2 mL